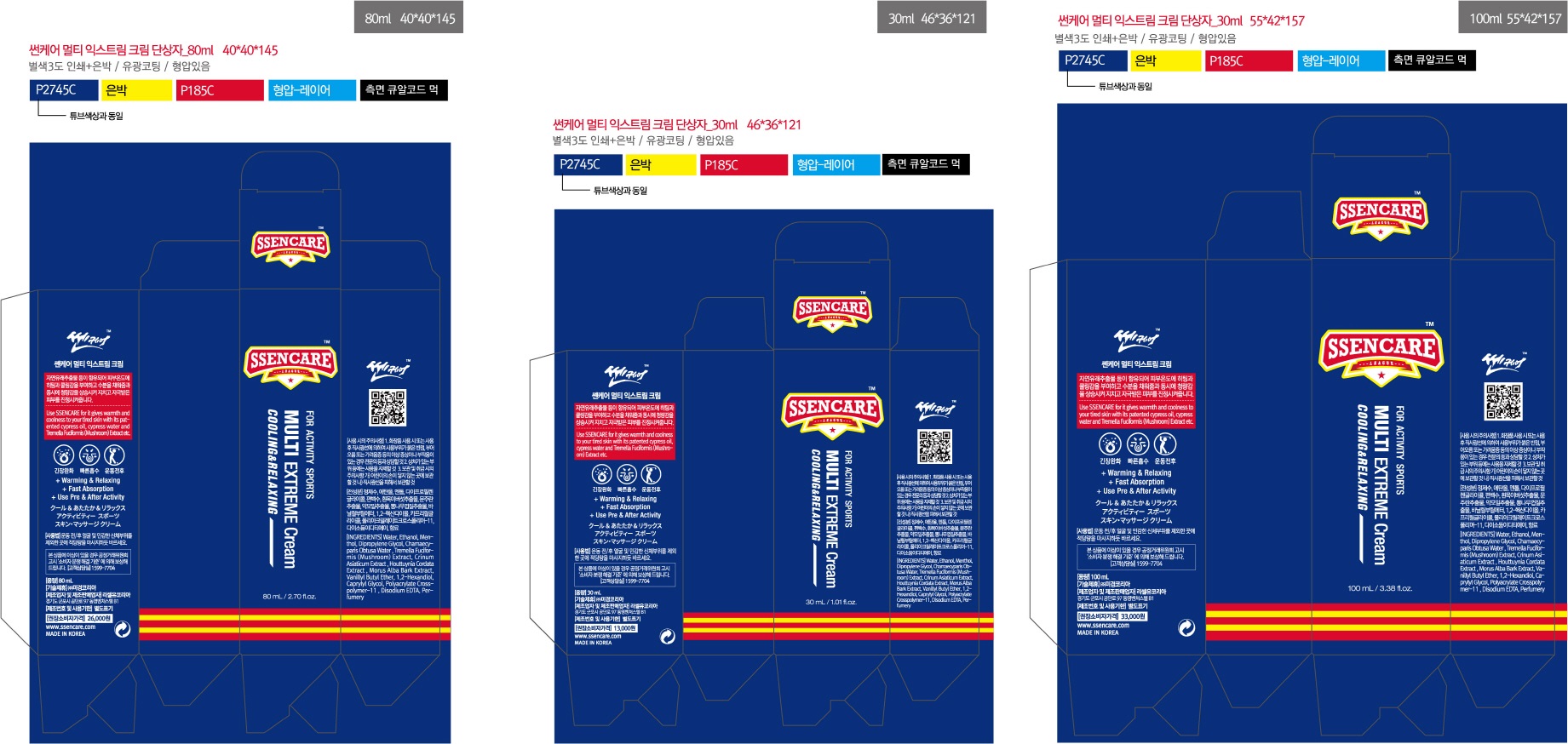 DRUG LABEL: SSENCARE
NDC: 72506-0001 | Form: LIQUID
Manufacturer: MIKYEONG KOREA CO.,LTD
Category: otc | Type: HUMAN OTC DRUG LABEL
Date: 20210406

ACTIVE INGREDIENTS: MENTHOL 4 g/100 mL
INACTIVE INGREDIENTS: WATER; VANILLYL BUTYL ETHER

ACTIVE INGREDIENT

Menthol

INACTIVE INGREDIENT

Vanillyl Butyl Ether, Water, etc

PURPOSE

Warming & Relaxing, Calming

WARNINGS

1. Do not use in the following cases(Eczema and scalp wounds)
2.Side Effects
1)Due to the use of this druf if rash, irritation, itching and symptopms of hypersnesitivity occur dicontinue use and consult your phamacisr or doctor
3.General Precautions
1)If in contact with the eyes, wash out thoroughty with water If the symptoms are servere, seek medical advice immediately
2)This product is for exeternal use only. Do not use for internal use
4.Storage and handling precautions
1)If possible, avoid direct sunlight and store in cool and area of low humidity
2)In order to maintain the quality of the product and avoid misuse
3)Avoid placing the product near fire and store out in reach of children

Keep out of reach of children.

INDICATIONS AND USAGE

Exercise before / after, except for sensitive areas, massage the appropriate amount as necessary

DOSAGE AND ADMINISTRATION

for external use only